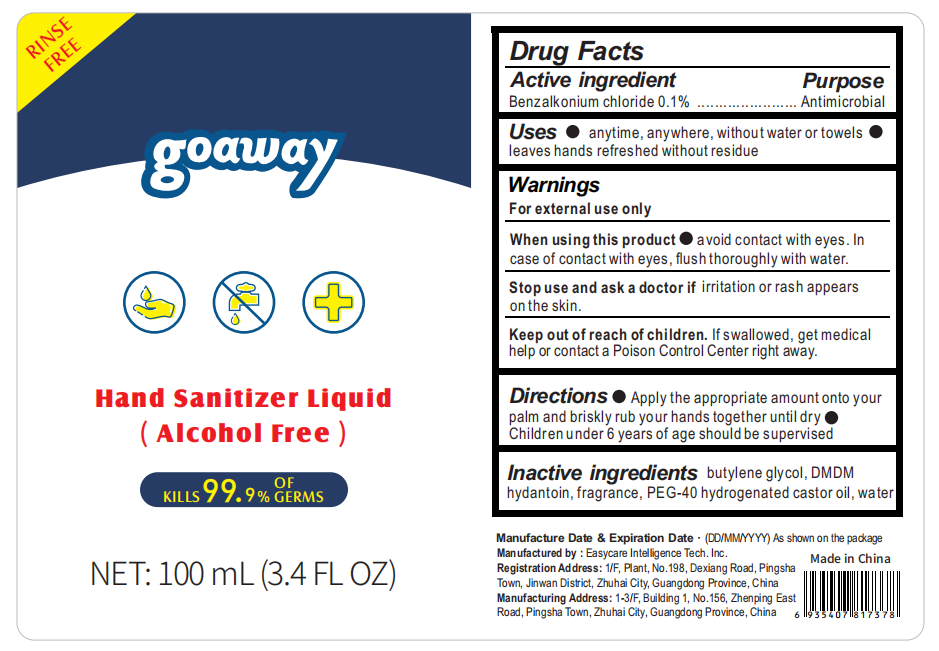 DRUG LABEL: Hand Sanitizer Liquid(Alcohol Free)
NDC: 56045-005 | Form: LIQUID
Manufacturer: Easycare Intelligence Tech. Inc.
Category: otc | Type: HUMAN OTC DRUG LABEL
Date: 20200420

ACTIVE INGREDIENTS: BENZALKONIUM CHLORIDE 0.114 mg/100 mL
INACTIVE INGREDIENTS: BUTYLENE GLYCOL; POLYOXYL 40 HYDROGENATED CASTOR OIL; DMDM HYDANTOIN; WATER

When using this product●avoid contact with eyes. In case of contact with eyes, flush thoroughly with water.
Stop use and ask a doctor if irritation or rash appears on the skin.

INACTIVE INGREDIENT

butylene glycol, DMDM hydantoin, fragrance, PEG-40 hydrogenated castor oil, water

PURPOSE

Disinfection
Sterilization
No Rinseing

keep out of reach of children

ACTIVE INGREDIENT

Benzalkonium chloride

INDICATIONS AND USAGE

●Apply the appropriate amount onto your palm and briskly rub your hands together until dry

●Children under 6 years of age should be supervised

DOSAGE AND ADMINISTRATION

●For external use only ●Flammable:Keep away from fire or flame